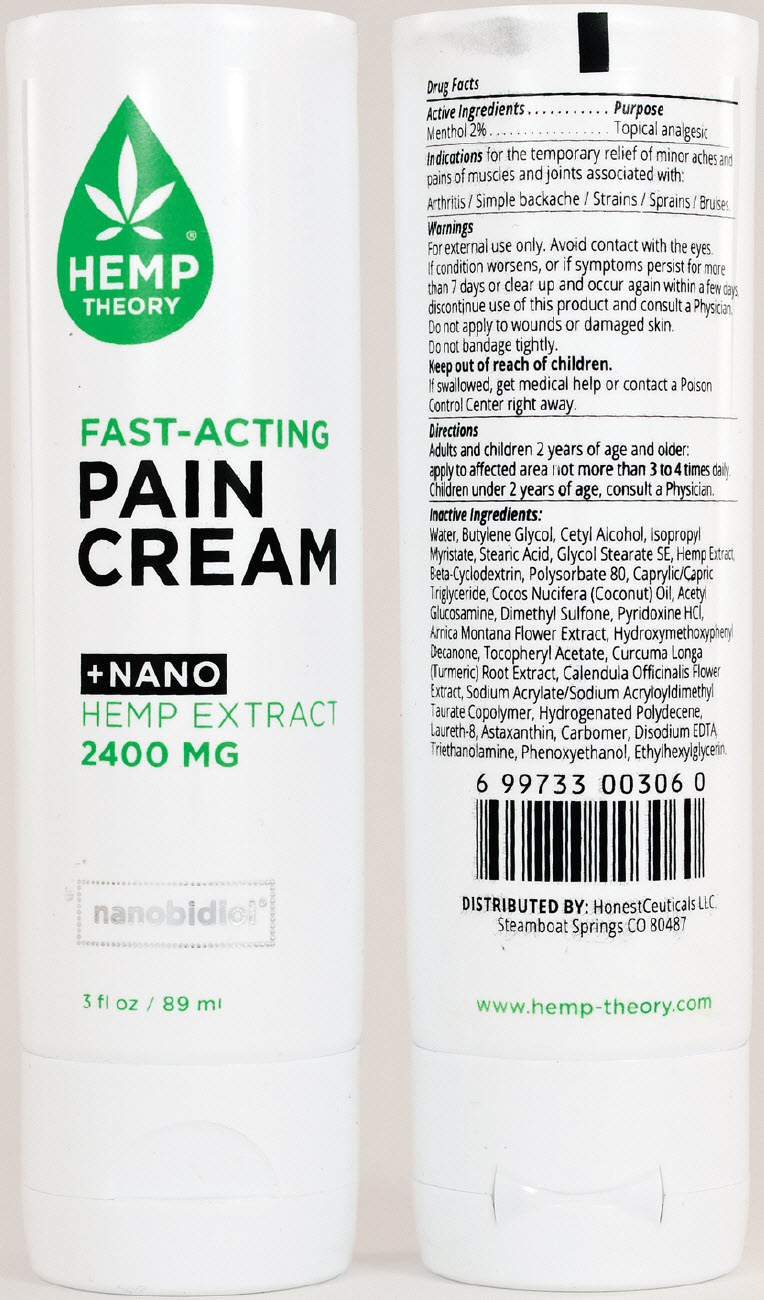 DRUG LABEL: Hemp Theory 
NDC: 64483-492 | Form: CREAM
Manufacturer: Clientele, Inc.
Category: otc | Type: HUMAN OTC DRUG LABEL
Date: 20191209

ACTIVE INGREDIENTS: MENTHOL, UNSPECIFIED FORM 2 mg/100 mL
INACTIVE INGREDIENTS: Water; Butylene Glycol; Cetyl Alcohol; Isopropyl Myristate; Stearic Acid; Glycol Stearate SE; APOCYNUM CANNABINUM ROOT; BETADEX; Polysorbate 80; MEDIUM-CHAIN TRIGLYCERIDES; COCONUT OIL; N-ACETYLGLUCOSAMINE; Dimethyl Sulfone; PYRIDOXINE HYDROCHLORIDE; ARNICA MONTANA FLOWER; 1-(4-HYDROXY-3-METHOXYPHENYL)-DECAN-3-ONE; .ALPHA.-TOCOPHEROL ACETATE; TURMERIC; CALENDULA OFFICINALIS FLOWER; SODIUM ACRYLATE/SODIUM ACRYLOYLDIMETHYLTAURATE COPOLYMER (4000000 MW); HYDROGENATED POLYDECENE (550 MW); C20-40 PARETH-3; Astaxanthin; CARBOMER HOMOPOLYMER, UNSPECIFIED TYPE; EDETATE DISODIUM; TROLAMINE; Phenoxyethanol; Ethylhexylglycerin

Hemp Theory®
Fast Acting Pain Cream

Drug Facts

Active Ingredients

Menthol 2%

Purpose

Topical analgesic

Indications

for the temporary relief of minor aches and pains of muscles and joints associated with:

Arthritis / Simple backache / Strains / Sprains / Bruises.

Warnings

For external use only. Avoid contact with the eyes.

If condition worsens, or if symptoms persist for more than 7 days or clear up and occur again within a few days, discontinue use of this product and consult a Physician.

Do not apply to wounds or damaged skin.

Do not bandage tightly.

Keep out of reach of children.

If swallowed, get medical help or contact a Poison Control Center right away.

Directions

Adults and children 2 years of age and older:
apply to affected area not more than 3 to 4 times daily.

Children under 2 years of age, consult a Physician.

Inactive Ingredients

Water, Butylene Glycol, Cetyl Alcohol, Isopropyl Myristate, Stearic Acid, Glycol Stearate SE, Hemp Extract, Beta-Cyclodextrin, Polysorbate 80, Caprylic/Capric Triglyceride, Cocos Nucifera (Coconut) Oil, Acetyl Glucosamine, Dimethyl Sulfone, Pyridoxine HCl, Arnica Montana Flower Extract, Hydroxymethoxphenyl Decanone, Tocopheryl Acetate, Curcuma Longa (Turmeric) Root Extract, Calendula Officinalis Flower Extract, Sodium Acrylate/Sodium Acryloyldimethyl Taurate Copolymer, Hydrogenated Polydecene, Laureth-8, Astaxanthin, Carbomer, Disodium EDTA, Triethanolamine, Phenoxyethanol, Ethylhexylglycerin.

DISTRIBUTED BY: HonestCeuticals LLC,
Steamboat Springs CO 80487

PRINCIPAL DISPLAY PANEL - 89 ml Tube

HEMP®
THEORY

FAST-ACTING
PAIN
CREAM

+NANO
HEMP EXTRACT
2400 MG

nanobidiol®

3 fl oz / 89 ml